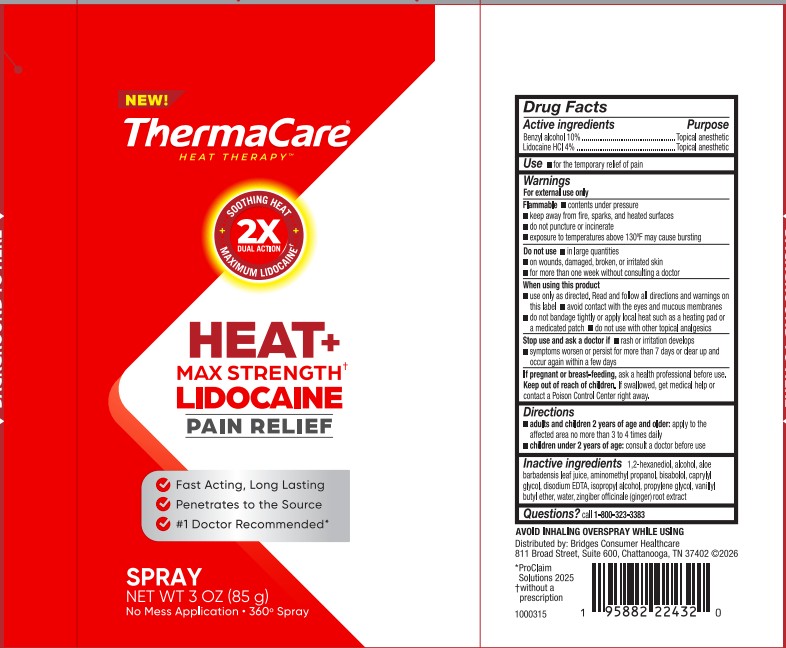 DRUG LABEL: Thermacare Max Strength Lidocaine
NDC: 69693-004 | Form: SPRAY
Manufacturer: Clarion Brands LLC
Category: otc | Type: HUMAN OTC DRUG LABEL
Date: 20251202

ACTIVE INGREDIENTS: LIDOCAINE HCL 4 g/100 mL; BENZYL ALCOHOL 10 g/100 mL
INACTIVE INGREDIENTS: GINGER; AMINOMETHYL PROPANOL; VANILLYL BUTYL ETHER; EDETATE DISODIUM; 1,2-HEXANEDIOL; ALCOHOL; ISOPROPYL ALCOHOL; PROPYLENE GLYCOL; CAPRYLYL GLYCOL; WATER; ALOE BARBADENSIS LEAF JUICE; BISABOLOL

ACTIVE INGREDIENT

Benzyl alcohol 10%

Lidocaine HCl 4%

PURPOSE

Topical anesthetic

Use

- for the termporary relief of pain

WARNINGS

For external use only

Flammable

- contents under pressure
- keep away from fire, sparks, and heated surfaces
- do not puncture or incinerate
- exposure to temperatures above 130ºF may cause bursting

Do not use

- in large quantities
- on wounds, damaged, broken, or irritated skin
- for more than one week without consulting a doctor

When using this product

- use only as directed. Read and follow all directions and warnings on this label
- avoid contact with the eyes and mucous membranes
- do not bandage tightly or apply local heat such as a heating pad or a medicated patch
- do not use with other topical analgesics

Stop use and ask a doctor if

- rash or irritation develops
- symptoms worsen or persist for more than 7 days or clear up and occur again within a few days

If pregnant or breast-feeding, ask a health professional before use.

Keep out of reach of children. If swallowed, get medical help or contact a Poison Control Center right away.

WHEN USING

- adults and children 2 years of age and older: apply to the affected area no more than 3 to 4 times daily
- children under 2 years of age: consult a doctor before use

INACTIVE INGREDIENT

1,2 hexanediol

alcohol

aloe barbadensis leaf juice

aminomethyl propanol

bisabolol

caprylyl glycol

disodium EDTA

isopropyl alcohol

propylene glycol

vanillyl butyl ether

water

zingiber officinale (ginger) root extract

QUESTIONS

1-800-323-3383

DOSAGE AND ADMINISTRATION

Benzyl alcohol 10%

Lidocaine HCl 4%

Directions

adults and children 2 years of age and older: apply to affected area no more than 3 to 4 times daily

children under 2 years of age: consult a doctor before use.

PACKAGE LABEL

NEW! ThermaCare Heat Therapy

Soothing Heat 2x Dual Action Maximum Lidocaine

Heat + Max Strength Lidocaine Pain Relief

Fast Acting, Long Lasting

Penetrates to the Source

Number 1 Doctor Recommended

Spray NET WT 3oz (85g)

No Mess Application - 360 Degree Spray

Distributed by: Bridges Consumer Healthcare

811 Broad Street, Suite 600, Chattanooga, TN 37402